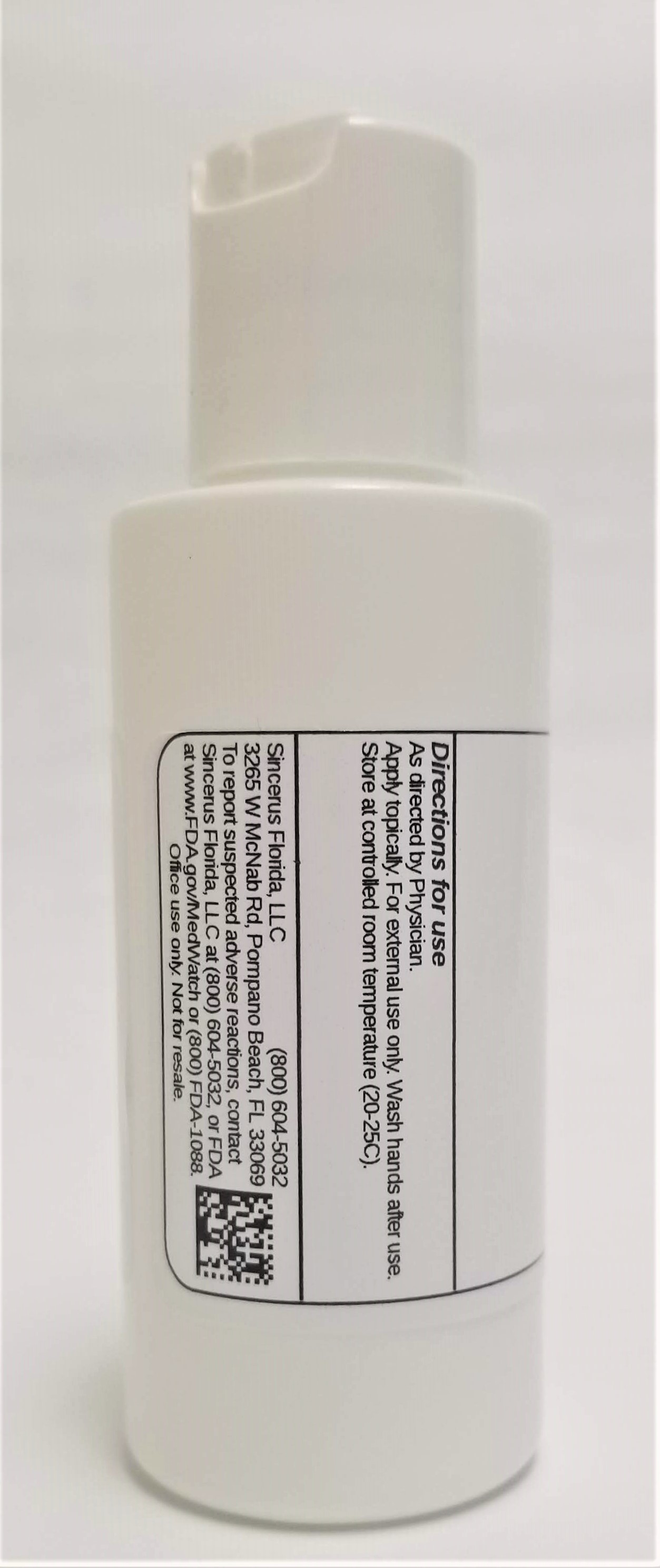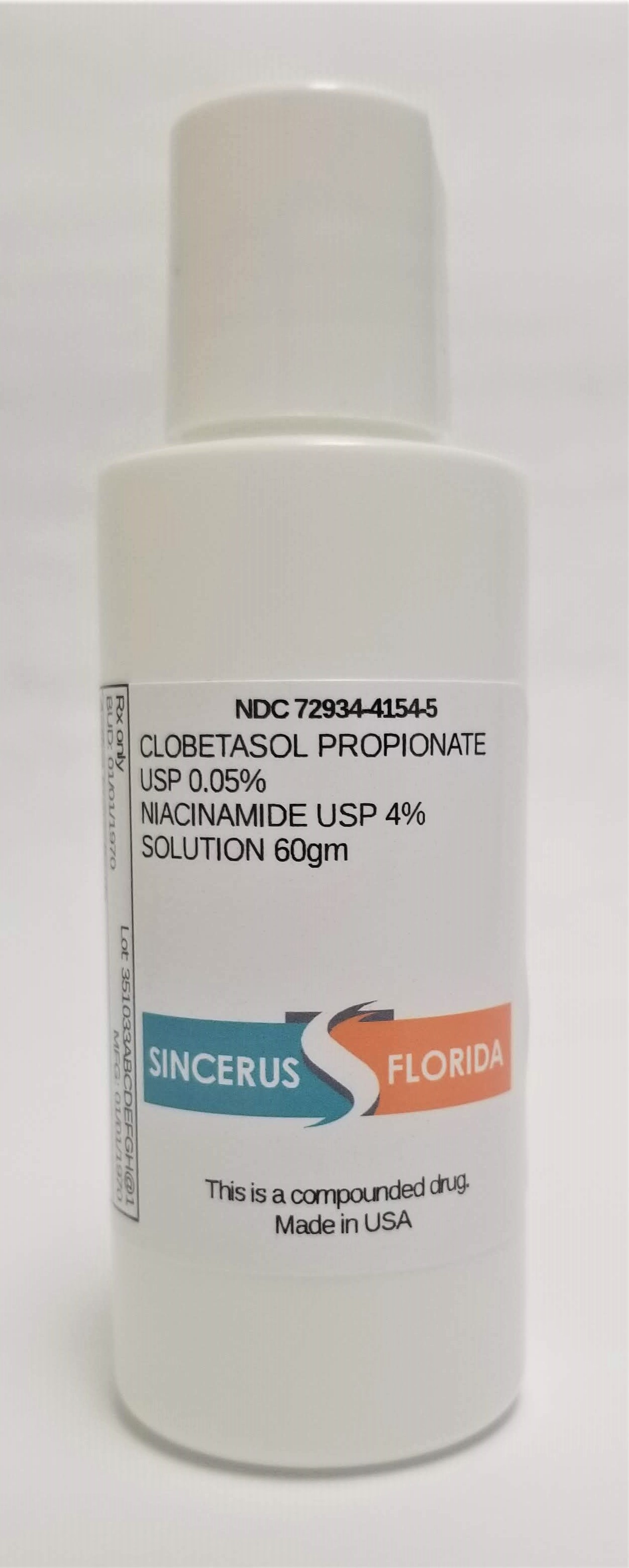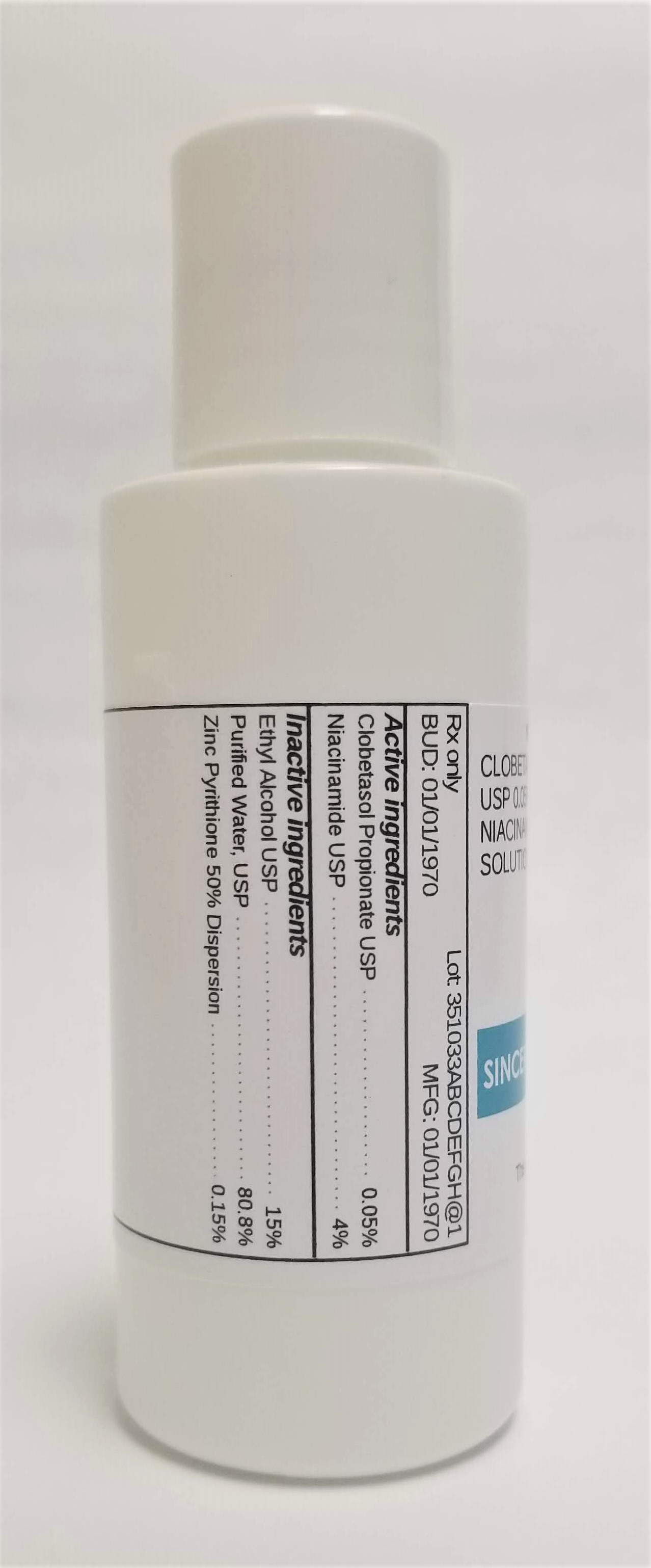 DRUG LABEL: NIACINAMIDE 4% / CLOBETASOL PROPIONATE 0.05%
NDC: 72934-4154 | Form: SOLUTION
Manufacturer: Sincerus Florida, LLC
Category: prescription | Type: HUMAN PRESCRIPTION DRUG LABEL
Date: 20190520

ACTIVE INGREDIENTS: CLOBETASOL PROPIONATE 0.05 g/100 g; NIACINAMIDE 4 g/100 g

NIACINAMIDE 4% / CLOBETASOL PROPIONATE 0.05%